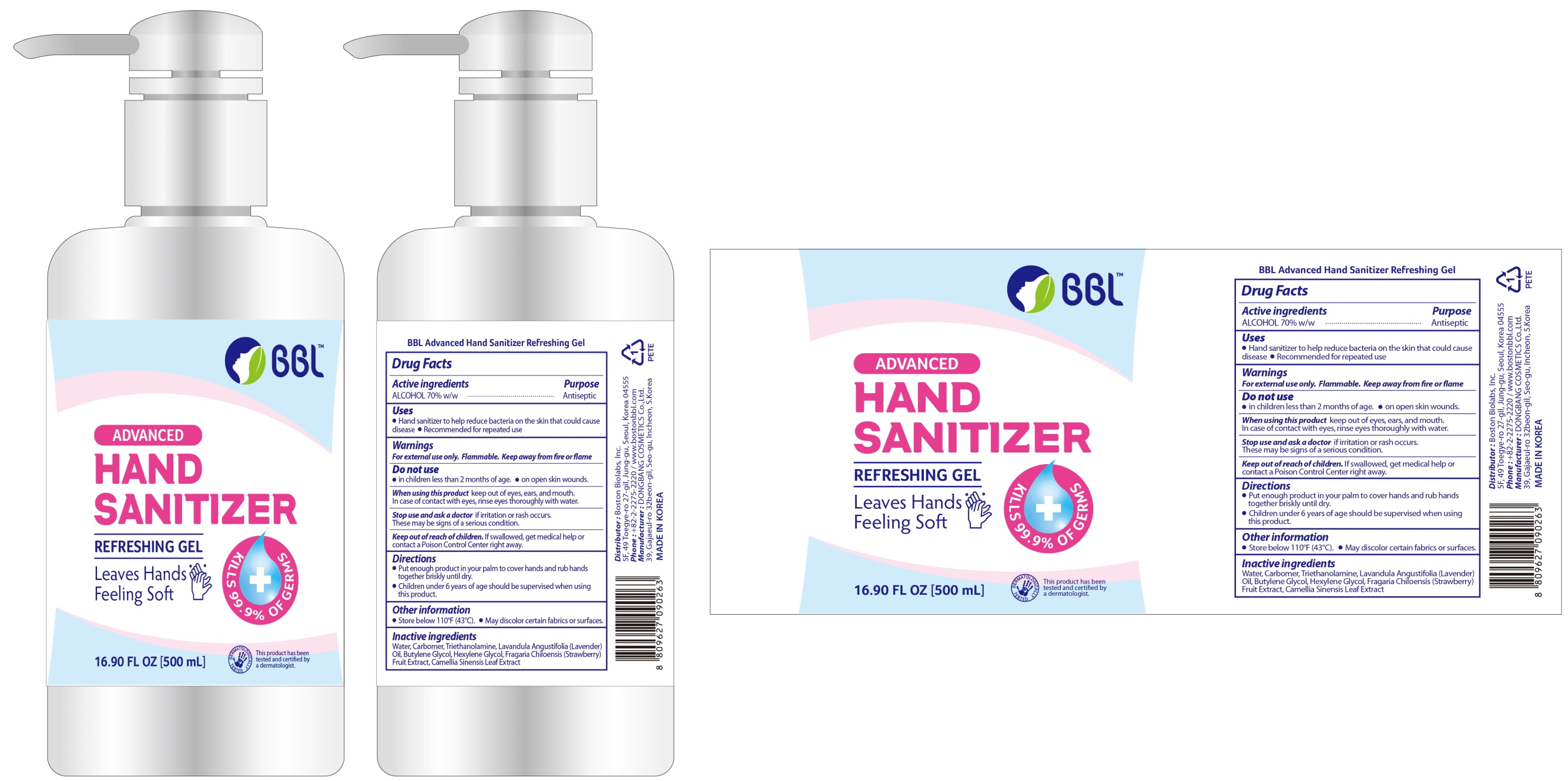 DRUG LABEL: BBL Advanced Hand Sanitizer Refreshing
NDC: 78579-010 | Form: GEL
Manufacturer: Boston Biolabs. Inc.
Category: otc | Type: HUMAN OTC DRUG LABEL
Date: 20200608

ACTIVE INGREDIENTS: ALCOHOL 350 g/500 mL
INACTIVE INGREDIENTS: Water; CARBOMER HOMOPOLYMER, UNSPECIFIED TYPE; TROLAMINE; LAVENDER OIL; Butylene Glycol; Hexylene Glycol; BEACH STRAWBERRY; GREEN TEA LEAF

ACTIVE INGREDIENT

ALCOHOL 70% w/w

INACTIVE INGREDIENTS

Water, Carbomer, Triethanolamine, Lavandula Angustifolia (Lavender) Oil, Butylene Glycol, Hexylene Glycol, Fragaria Chiloensis (Strawberry) Fruit Extract, Camellia Sinensis Leaf Extract

PURPOSE

Antiseptic

WARNINGS

For external use only. Flammable. Keep away from fire or flame.
--------------------------------------------------------------------------------------------------------
Do not use
• in children less than 2 months of age.
• on open skin wounds.
--------------------------------------------------------------------------------------------------------
When using this product keep out of eyes, ears, and mouth. In case of contact with eyes, rinse eyes thoroughly with water.
--------------------------------------------------------------------------------------------------------
Stop use and ask a doctor if irritation or rash occurs. These may be signs of a serious condition.

KEEP OUT OF REACH OF CHILDREN

If swallowed, get medical help or contact a Poison Control Center right away.

Uses

• Hand sanitizer to help reduce bacteria on the skin that could cause disease.

• Recommended for repeated use.

Directions

• Put enough product in your palm to cover hands and rub hands together briskly until dry.
• Children under 6 years of age should be supervised when using this product.

Other information

• Store below 110°F (43°C).
• May discolor certain fabrics or surfaces.